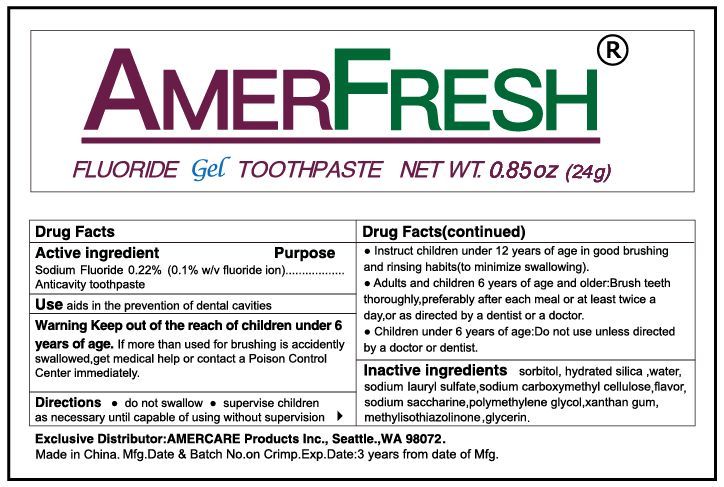 DRUG LABEL: Amerfresh
NDC: 70766-002 | Form: PASTE
Manufacturer: Yangzhou SION Commodity Co.,Ltd
Category: otc | Type: HUMAN OTC DRUG LABEL
Date: 20231208

ACTIVE INGREDIENTS: SODIUM FLUORIDE 0.22 g/100 g
INACTIVE INGREDIENTS: SACCHARIN SODIUM; METHYLISOTHIAZOLINONE; POLYETHYLENE GLYCOL 1000; DISODIUM CARBOXYMETHYLARSONATE; SORBITOL; XANTHAN GUM; METHYLENE GLYCOL; WATER; GLYCERIN; SODIUM LAURYL SULFATE; HYDRATED SILICA

Amerfresh Fluoride Toothpaste

Active ingredients

sodium fluoride 0.22%(0.1% w/v fluoride ion)

Purpose

anticavity

Uses

aids in the prevention of dental cavities.

Warnings

Keep out of the reach of children under 6 years of age.if more than used for brushing is accidently swallowed,get medical help or contact a Poison Control Center immediately.

Keep out of reach of children.

Directions

do not swallow .

supervise children as necessary until capable of useing without supervision

instruct children under 12 years of age in good brushing and rinsing habits(to minimize swallowing).

Adults and children 6 years of age and older:Brush teeth thoroughly,preferably after each meal or at least twice a day,or as directed by a dentist or a physician.

Children under 6 years of age:do not use unless directed by a doctor or dentist.

INACTIVE INGREDIENT

sorbitol,polyethylene glycol,sodium carboxymethyl cellulose ,xanthan gum,hydrated silica,glycerin,sacchairn sodium,sodium lauryl sulfate,water,methylisothiazolinone